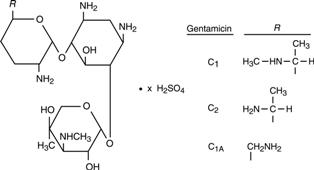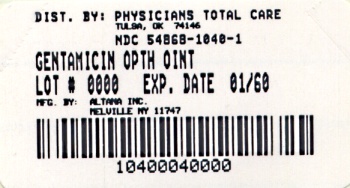 DRUG LABEL: Gentamicin Sulfate
NDC: 54868-1040 | Form: OINTMENT
Manufacturer: Physicians Total Care, Inc.
Category: prescription | Type: HUMAN PRESCRIPTION DRUG LABEL
Date: 20100607

ACTIVE INGREDIENTS: GENTAMICIN SULFATE 3 mg/1 g
INACTIVE INGREDIENTS: PETROLATUM; MINERAL OIL

Rx only

DESCRIPTION

Gentamicin sulfate is a water soluble antibiotic of the aminoglycoside group.

Gentamicin Sulfate Ophthalmic Ointment USP is a sterile ointment for topical ophthalmic use. Each gram contains gentamicin sulfate (equivalent to 3 mg gentamicin) in a base of white petrolatum and mineral oil.

Gentamicin is obtained from cultures of Micromonospora purpurea. Gentamicin sulfate is a mixture of the sulfate salts of gentamicin C1, C2 and C1A. All three components appear to have similar antimicrobial activities. Gentamicin sulfate occurs as a white powder and is soluble in water and insoluble in alcohol. The structural formula is as follows:

CLINICAL PHARMACOLOGY

Microbiology: Gentamicin sulfate is active in vitro against many strains of the following microorganisms:

Staphylococcus aureus, Staphylococcus epidermidis, Streptococcus pyogenes, Streptococcus pneumoniae, Enterobacter aerogenes, Escherichia coli, Haemophilus influenzae, Klebsiella pneumoniae, Neisseria gonorrhoeae, Pseudomonas aeruginosa, and Serratia marcescens.

INDICATIONS AND USAGE

Gentamicin Sulfate Ophthalmic Ointment is indicated in the topical treatment of ocular bacterial infections, including conjunctivitis, keratitis, keratoconjunctivitis, corneal ulcers, blepharitis, blepharoconjunctivitis, acute meibomianitis, and dacryocystitis caused by susceptible strains of the following microorganisms:

Staphylococcus aureus, Staphylococcus epidermidis, Streptococcus pyogenes, Streptococcus pneumoniae, Enterobacter aerogenes, Escherichia coli, Haemophilus influenzae, Klebsiella pneumoniae, Neisseria gonorrhoeae, Pseudomonas aeruginosa, and Serratia marcescens.

CONTRAINDICATIONS

Gentamicin Sulfate Ophthalmic Ointment is contraindicated in patients with known hypersensitivity to any of the components.

WARNINGS

NOT FOR INJECTION INTO THE EYE. Gentamicin Sulfate Ophthalmic Ointment is not for injection. It should never be injected subconjunctivally, nor should it be directly introduced into the anterior chamber of the eye.

PRECAUTIONS

General: Prolonged use of topical antibiotics may give rise to overgrowth of non-susceptible organisms including fungi. Bacterial resistance to gentamicin may also develop. If purulent discharge, inflammation or pain becomes aggravated, the patient should discontinue use of the medication and consult a physician.

If irritation or hypersensitivity to any component of the drug develops, the patient should discontinue use of this preparation, and appropriate therapy should be instituted.

Ophthalmic ointments may retard corneal healing.

Information For Patients: To avoid contamination, do not touch tip of container to the eye, eyelid, or any surface.

Carcinogenesis, Mutagenesis and Impairment of Fertility: There are no published carcinogenicity or impairment of fertility studies on gentamicin. Aminoglycoside antibiotics have been found to be non-mutagenic.

Pregnancy: Teratogenic effects - Pregnancy Category C. Gentamicin has been shown to depress body weights, kidney weights, and median glomerular counts in newborn rats when administered systemically to pregnant rats in daily doses approximately 500 times the maximum recommended ophthalmic human dose. There are no adequate and well-controlled studies in pregnant women. Gentamicin should be used during pregnancy only if the potential benefit justifies the potential risk to the fetus.

Pediatric Use: Safety and effectiveness in neonates have not been established.

ADVERSE REACTIONS

Bacterial and fungal corneal ulcers have developed during treatment with gentamicin ophthalmic preparations.

The most frequently reported adverse reactions are ocular burning and irritation upon drug instillation, non-specific conjunctivitis, conjunctival epithelial defects, and conjunctival hyperemia.

Other adverse reactions which have occurred rarely are allergic reactions, thrombocytopenic purpura, and hallucinations.

DOSAGE AND ADMINISTRATION

Apply a small amount (about ½ inch) to the affected eye(s) two to three times a day.

HOW SUPPLIED

Gentamicin Sulfate Ophthalmic Ointment USP (equivalent to 3 mg gentamicin) is supplied as follows:

NDC 54868-1040-1 3.5 gram tubes

Store at 25°C (77°F); excursions permitted to 15-30°C (59-86°F)
[see USP Controlled Room Temperature].

E. FOUGERA & CO.
a division of Altana Inc.
MELVILLE, NEW YORK 11747

I24438A
R4/03
#82

Relabeling of "Additional Barcode" by:
Physicians Total Care, Inc.
Tulsa, OK 74146

PRINCIPAL DISPLAY PANEL

Gentamicin Sulfate Ophthalmic Ointment USP